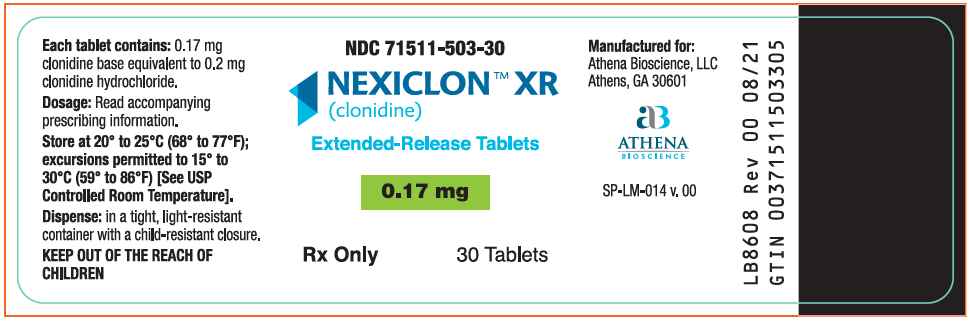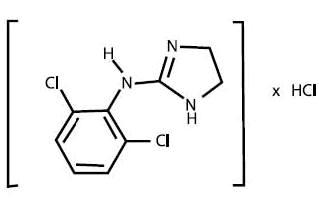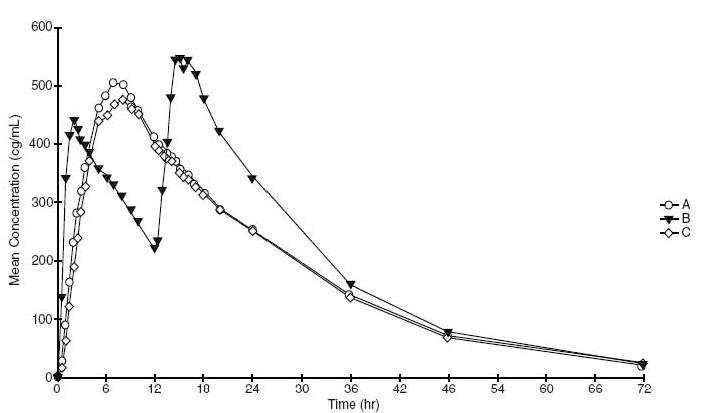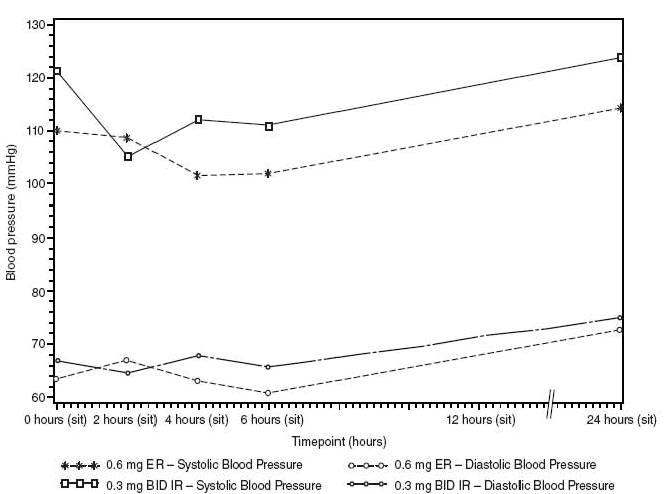 DRUG LABEL: Nexiclon XR
NDC: 71511-503 | Form: TABLET, EXTENDED RELEASE
Manufacturer: Athena Bioscience, LLC
Category: prescription | Type: HUMAN PRESCRIPTION DRUG LABEL
Date: 20220322

ACTIVE INGREDIENTS: CLONIDINE 0.17 mg/1 1
INACTIVE INGREDIENTS: CROSPOVIDONE; SODIUM SILICATE; LACTOSE MONOHYDRATE; MAGNESIUM STEARATE; CELLULOSE, MICROCRYSTALLINE; VINYL ACETATE; POVIDONE; SODIUM POLYSTYRENE SULFONATE; TRIACETIN; HYPROMELLOSE, UNSPECIFIED; POLYETHYLENE GLYCOL 1000; TITANIUM DIOXIDE

HIGHLIGHTS OF PRESCRIBING INFORMATION

NEXICLON™ XR (clonidine) Extended-Release Tablets
These highlights do not include all the information needed to use NEXICLON™ XR (clonidine) Extended-Release Tablets safely and effectively. See full prescribing information for NEXICLON™ XR (clonidine) Extended-Release Tablets.
NEXICLON™ XR (clonidine) Extended-Release Tablets
Initial U.S. Approval: 1974

1 INDICATIONS AND USAGE

NEXICLON XR is a central alpha-adrenergic agonist indicated for:

- Treatment of hypertension (1)

2 DOSAGE AND ADMINISTRATION

- Initial dose: 0.17 mg once daily. Elderly patients may benefit from a lower initial dose. Initial dose is recommended to be administered at bedtime. (2.1)
- Maintenance dose: Further increments of 0.09 mg once daily may be made at weekly intervals if necessary until the desired response is achieved. The therapeutic doses most commonly employed have ranged from 0.17 mg to 0.52 mg once daily. (2.2)
- Patients with renal impairment: Up-titrate slowly (2.4)

3 DOSAGE FORMS AND STRENGTHS

Extended-Release Tablets: 0.17, 0.26 mg clonidine base

4 CONTRAINDICATIONS

- Known hypersensitivity to clonidine (rash, angioedema) (4)

5 WARNINGS AND PRECAUTIONS

- Patients should not discontinue therapy without consulting a physician. Dose reduction should be performed gradually over a 2- to 4-day period to avoid withdrawal symptomatology. Rare instances of hypertensive encephalopathy, cerebrovascular accidents and death have been reported after clonidine withdrawal. (5.1)
- Monitor closely and up-titrate slowly in patients with severe coronary insufficiency, conduction disturbances, recent myocardial infarction, cerebrovascular disease, or chronic renal failure. (5.2)
- Patients who engage in potentially hazardous activities, such as operating machinery or driving, should be advised of a possible sedative effect of clonidine. (5.2)
- In perioperative use, NEXICLON XR may be administered up to 28 hours prior to surgery and resumed the following day. (5.3)

6 ADVERSE REACTIONS

There is very little experience with NEXICLON XR in controlled trials. Based on this limited experience, the adverse event profile appears similar with the immediate-release clonidine formulation. The most commonly expected adverse reactions are dry mouth, drowsiness, and dizziness. (6)

To report SUSPECTED ADVERSE REACTIONS, contact Athena Bioscience LLC at 1-833-874-2664 and www.athenabioscience.com or FDA at 1-800-FDA-1088 or www.fda.gov/medwatch.

7 DRUG INTERACTIONS

- Sedating drugs: Clonidine may potentiate the CNS-depressive effects of alcohol, barbiturates or other sedating drugs. (7)
- Tricyclic antidepressants: May reduce the hypotensive effect of clonidine, necessitating an increase in clonidine dose. (7)
- Drugs known to affect sinus node function or AV nodal conduction (e.g., digitalis, calcium channel blockers, beta-blockers): Additive effects such as bradycardia and AV block. (7)

8 USE IN SPECIFIC POPULATIONS

- Pregnancy Category C (8.1)
- Clonidine is secreted in human milk. (8.2)
- Safety and effectiveness in children have not been established. (8.3)
- Renal impairment: Dose may need adjustment. (2.4)

FULL PRESCRIBING INFORMATION

1 INDICATIONS AND USAGE

NEXICLON XR is indicated in the treatment of hypertension. NEXICLON XR may be employed alone or concomitantly with other antihypertensive agents.

2 DOSAGE AND ADMINISTRATION

The dose of NEXICLON XR must be adjusted according to the patient's individual blood pressure response. The following is a general guide to its administration in adults.

2.1 Initial Dose

Dosing with NEXICLON XR should be initiated at 0.17 mg once daily. Elderly patients may benefit from a lower initial dose [ see Use in Specific Populations (8.4)]. Initial dose is recommended to be administered at bedtime.

2.2 Maintenance Dose

Further increments of 0.09 mg once daily may be made at weekly intervals if necessary until the desired response is achieved. The therapeutic doses most commonly employed have ranged from 0.17 mg to 0.52 mg once daily.

NEXICLON XR was studied at doses of 0.17 to 0.52 mg once daily. Doses higher than 0.52 mg per day were not evaluated and are not recommended.

2.3 Patients Currently Using Clonidine Hydrochloride Immediate-Release Tablets

The recommended dose of NEXICLON XR for patients who are currently taking clonidine hydrochloride immediate-release tablets is provided in the table below.

 | NEXICLON XR (clonidine) Extended-Release Tablets | Equivalent dose of Clonidine HCl Immediate-Release Tablets
Initial Dose | 0.17 mg once daily | 0.1 mg twice daily
Maintenance Dose Titration Increments | 0.09 mg once daily | 0.05 mg twice daily
Common Doses Used for Blood Pressure Effect | 0.17 mg once daily | 0.1 mg twice daily
Common Doses Used for Blood Pressure Effect | 0.34 mg once daily | 0.2 mg twice daily
Common Doses Used for Blood Pressure Effect | 0.52 mg once daily | 0.3 mg twice daily

2.4 Renal Impairment

Adjust dosage according to the degree of impairment. In patients with end stage kidney disease on maintenance dialysis, start at 0.09 mg per day and up-titrate slowly to minimize dose related adverse events.

Monitor patients carefully, especially for bradycardia, sedation and hypotension. Only a minimal amount of clonidine is removed during routine hemodialysis.

In patients with moderate to severe kidney impairment not undergoing dialysis, initiate clonidine at the same dose as for patients without renal impairment. Up-titrate slowly and monitor for dose-related adverse events.

3 DOSAGE FORMS AND STRENGTHS

0.17 mg Extended-Release Tablets (clonidine base)

0.26 mg Extended-Release Tablets (clonidine base)

4 CONTRAINDICATIONS

NEXICLON XR should not be used in patients with known hypersensitivity to clonidine [ see Warnings and Precautions (5.2)].

5 WARNINGS AND PRECAUTIONS

5.1 Withdrawal

Instruct patients not to discontinue therapy without consulting their physician. Sudden cessation of clonidine treatment has resulted in symptoms such as nervousness, agitation, headache, and tremor accompanied or followed by a rapid rise in blood pressure and elevated catecholamine concentrations in the plasma. The likelihood of such reactions to discontinuation of clonidine therapy appears to be greater after administration of higher doses or continuation of concomitant beta-blocker treatment and special caution is therefore advised in these situations. Rare instances of hypertensive encephalopathy, cerebrovascular accidents and death have been reported after clonidine withdrawal. When discontinuing therapy with NEXICLON XR, reduce the dose gradually over 2 to 4 days to avoid withdrawal symptoms.

An excessive rise in blood pressure following discontinuation of NEXICLON XR can be reversed by administration of oral clonidine hydrochloride or by intravenous phentolamine. If therapy is to be discontinued in patients receiving a beta-blocker and clonidine concurrently, the beta-blocker should be withdrawn several days before the gradual discontinuation of NEXICLON XR.

Because children commonly have gastrointestinal illnesses that lead to vomiting, they may be particularly susceptible to hypertensive episodes resulting from abrupt inability to take medication.

5.2 General Precautions

In patients who have developed localized contact sensitization to a clonidine transdermal system, substitution of oral clonidine therapy may be associated with the development of a generalized skin rash.

In patients who develop an allergic reaction to a clonidine transdermal system, substitution of oral clonidine may also elicit an allergic reaction (including generalized rash, urticaria, or angioedema).

Monitor carefully and up-titrate slowly in patients with severe coronary insufficiency, conduction disturbances, recent myocardial infarction, cerebrovascular disease, or chronic renal failure.

Patients who engage in potentially hazardous activities, such as operating machinery or driving, should be advised of a possible sedative effect of clonidine. The sedative effect may be increased by concomitant use of alcohol, barbiturates, or other sedating drugs.

5.3 Perioperative Use

NEXICLON XR may be administered up to 28 hours prior to surgery and resumed the following day. Blood pressure should be carefully monitored during surgery and additional measures to control blood pressure should be available if required.

6 ADVERSE REACTIONS

The following serious adverse reactions are discussed in detail elsewhere in the labeling:

- Withdrawal [ see Warnings and Precautions (5.1)]
- Allergic reactions [ see Warnings and Precautions (5.2)]

6.1 NEXICLON XR Clinical Trial Experience

There is very limited experience with NEXICLON XR in controlled trials. Based on this limited experience, the adverse event profile appears similar with to the immediate-release clonidine formulation.

6.2 Experience with Immediate-Release Clonidine

Most adverse reactions are mild and tend to diminish with continued therapy. The most frequent (which also appear to be dose-related) are dry mouth (approximately 40%); drowsiness (approximately 33%); dizziness (approximately 16%); constipation and sedation (approximately 10% each).

The following less frequent adverse reactions have also been reported in patients receiving immediate-release clonidine, but in many cases patients were receiving concomitant medication and a causal relationship has not been established.

Body as a Whole: Fatigue, fever, headache, pallor, weakness, and withdrawal syndrome. Also reported were a weakly positive Coombs’ test and increased sensitivity to alcohol.

Cardiovascular: Bradycardia, congestive heart failure, electrocardiographic abnormalities (i.e., sinus node arrest, junctional bradycardia, high degree AV block and arrhythmias), orthostatic symptoms, palpitations, Raynaud’s phenomenon, syncope, and tachycardia. Cases of sinus bradycardia and atrioventricular block have been reported, both with and without the use of concomitant digitalis.

Central Nervous System (CNS): Agitation, anxiety, delirium, delusional perception, hallucinations (including visual and auditory), insomnia, mental depression, nervousness, other behavioral changes, paresthesia, restlessness, sleep disorder, and vivid dreams or nightmares.

Dermatological: Alopecia, angioneurotic edema, hives, pruritus, rash, and urticaria.

Gastrointestinal: Abdominal pain, anorexia, constipation, hepatitis, malaise, mild transient abnormalities in liver function tests, nausea, parotitis, pseudo-obstruction (including colonic pseudo-obstruction), salivary gland pain, and vomiting.

Genitourinary: Decreased sexual activity, difficulty in micturition, erectile dysfunction, loss of libido, nocturia, and urinary retention.

Hematologic: Thrombocytopenia.

Metabolic: Gynecomastia, transient elevation of blood glucose or serum creatine phosphokinase, and weight gain.

Musculoskeletal: Leg cramps and muscle or joint pain.

Oro-otolaryngeal: Dryness of the nasal mucosa.

Ophthalmological: Accommodation disorder, blurred vision, burning of the eyes, decreased lacrimation, and dryness of eyes.

7 DRUG INTERACTIONS

No drug interaction studies have been conducted with NEXICLON XR. The following have been reported with other oral formulations of clonidine.

Clonidine may potentiate the CNS-depressive effects of alcohol, barbiturates or other sedating drugs. If a patient receiving clonidine hydrochloride is also taking tricyclic antidepressants, the hypotensive effect of clonidine may be reduced, necessitating an increase in the clonidine dose.

Monitor heart rate in patients receiving clonidine concomitantly with agents known to affect sinus node function or AV nodal conduction, e.g., digitalis, calcium channel blockers, and beta-blockers. Sinus bradycardia resulting in hospitalization and pacemaker insertion has been reported in association with the use of clonidine concomitantly with diltiazem or verapamil.

Amitriptyline in combination with clonidine enhances the manifestation of corneal lesions in rats [ see Nonclinical Toxicology (13.2)].

Alcohol: Based on in vitro studies, high concentration of alcohol may increase the rate of release of NEXICLON XR.

8 USE IN SPECIFIC POPULATIONS

8.1 Pregnancy

Pregnancy Category C. Reproduction studies performed in rabbits at doses up to approximately 3 times the oral maximum recommended daily human dose (MRDHD) of clonidine hydrochloride produced no evidence of a teratogenic or embryotoxic potential in rabbits. In rats, however, doses as low as 1/3 the oral MRDHD (1/15 the MRDHD on a mg/m^2 basis) of clonidine were associated with increased resorptions in a study in which dams were treated continuously from 2 months prior to mating. Increased resorptions were not associated with treatment at the same time or at higher dose levels (up to 3 times the oral MRDHD) when the dams were treated on gestation days 6 to 15. Increases in resorption were observed at much higher dose levels (40 times the oral MRDHD on a mg/kg basis; 4 to 8 times the MRDHD on a mg/m^2 basis) in mice and rats treated on gestation days 1 to 14 (lowest dose employed in the study was 500 mcg/kg).

No adequate, well-controlled studies have been conducted in pregnant women. Because animal reproduction studies are not always predictive of human response, this drug should be used during pregnancy only if clearly needed.

8.2 Nursing Mothers

Clonidine is secreted in human milk.

8.3 Pediatric Use

Safety and effectiveness in pediatric patients have not been established.

8.4 Geriatric Use

Elderly patients may benefit from a lower initial dose [ see Dosage and Administration (2)].

8.5 Patients with Renal Impairment

The initial dosage should be based on the degree of impairment. Monitor patients carefully for hypotension and bradycardia, and titrate to higher doses cautiously. Only a minimal amount of clonidine is removed during routine hemodialysis.

10 OVERDOSAGE

Hypertension may develop early and may be followed by hypotension, bradycardia, respiratory depression, hypothermia, drowsiness, decreased or absent reflexes, weakness, irritability and miosis. The frequency of CNS depression may be higher in children than adults. Large overdoses may result in reversible cardiac conduction defects or dysrhythmias, apnea, coma, and seizures. Signs and symptoms of overdose generally occur within 30 minutes to two hours after exposure. As little as 0.1 mg of clonidine has produced signs of toxicity in children.

There is no specific antidote for clonidine overdosage. Clonidine overdosage may result in the rapid development of CNS depression; therefore, induction of vomiting with ipecac syrup is not recommended. Gastric lavage may be indicated following recent and/or large ingestions. Administration of activated charcoal and/or a cathartic may be beneficial. Supportive care may include atropine sulfate for bradycardia, intravenous fluids and/or vasopressor agents for hypotension and vasodilators for hypertension. Naloxone may be a useful adjunct for the management of clonidine-induced respiratory depression, hypotension and/or coma; blood pressure should be monitored since the administration of naloxone has occasionally resulted in paradoxical hypertension. Tolazoline administration has yielded inconsistent results and is not recommended as first-line therapy. Dialysis is not likely to significantly enhance the elimination of clonidine.

The largest overdose reported to date involved a 28-year old male who ingested 100 mg of clonidine hydrochloride powder. This patient developed hypertension followed by hypotension, bradycardia, apnea, hallucinations, semicoma, and premature ventricular contractions. The patient fully recovered after intensive treatment. Plasma clonidine levels were 60 ng/mL after 1 hour, 190 ng/mL after 1.5 hours, 370 ng/mL after 2 hours, and 120 ng/mL after 5.5 and 6.5 hours. In mice and rats, the oral LD50 of clonidine is 206 and 465 mg/kg, respectively.

11 DESCRIPTION

NEXICLON XR (clonidine) Extended-Release Tablets are available for oral administration in two dose strengths: 0.17 mg and 0.26 mg. The 0.17 mg and 0.26 mg tablets are equivalent to 0.2 mg and 0.3 mg of immediate-release clonidine hydrochloride, respectively.

Clonidine hydrochloride, a centrally active alpha-adrenergic agonist, is an imidazoline derivative and exists as a mesomeric compound. The chemical name is 2-(2.6-dichlorophenylamino)-2-imidazoline hydrochloride. The following is the structural formula:

C9H9Cl2N3·HCl Mol. Wt. 266.56

Clonidine hydrochloride is an odorless, bitter, white crystalline substance soluble in water and alcohol.

The inactive ingredients are: crospovidone, dental-type silica, lactose monohydrate, magnesium stearate, microcrystalline cellulose, polyvinyl acetate, povidone, sodium polystyrene sulfonate, triacetin. The 0.17 mg tablet also contains hypromellose, polyethylene glycol, and titanium dioxide. The 0.26 mg tablet also contains D&C yellow #10 aluminum lake, FD&C yellow #6 aluminum lake, fractionated coconut oil, maltodextrin, polydextrose, talc, and titanium dioxide.

12 CLINICAL PHARMACOLOGY

12.1 Mechanism of Action

Clonidine stimulates alpha-adrenoreceptors in the brain stem. This action results in reduced sympathetic outflow from the central nervous system and in decreases in peripheral resistance, renal vascular resistance, heart rate, and blood pressure. The patient’s maximum blood pressure decrease occurred within 6 to 8 hours. Renal blood flow and glomerular filtration rate remain essentially unchanged. Normal postural reflexes are intact; therefore, orthostatic symptoms are mild and infrequent.

12.2 Pharmacodynamics

NEXICLON XR was studied in an open-label crossover, force titration, partially randomized trial in patients with mild and moderate essential hypertension who were on two or fewer antihypertensive medications. The trial was designed to compare steady-state exposures between the NEXICLON XR and clonidine immediate-release tablets. There were up- and down-titration phases. There was no washout period between phases or treatments.

Studies with immediate-release clonidine hydrochloride have demonstrated a moderate reduction (15% to 20%) in cardiac output in the supine position with no change in the peripheral resistance. At a 45° tilt, there is a smaller reduction in cardiac output and a decrease of peripheral resistance. During long-term therapy, cardiac output tends to return to control values, while peripheral resistance remains decreased. Slowing of the pulse rate has been observed in most patients given clonidine, but the drug does not alter normal hemodynamic response to exercise.

Tolerance to the antihypertensive effect may develop in some patients, necessitating a re-evaluation of therapy.

Other studies in patients have provided evidence of a reduction in plasma renin activity and in the excretion of aldosterone and catecholamines. The exact relationship of these pharmacologic actions to the antihypertensive effect of clonidine has not been fully elucidated.

Clonidine acutely stimulates growth hormone release in both children and adults, but does not produce a chronic elevation of growth hormone with long-term use.

12.3 Pharmacokinetics

Following single doses of NEXICLON XR 0.17 mg, clonidine mean (S.D.) peak plasma concentrations of 0.49 (±0.09) ng/mL occurred at 7.8 (±1.7) hours. The plasma half-life of clonidine was 13.7 (±3.0) hours. There was no effect of food on the pharmacokinetic parameters.

A = NEXICLON XR Tablets (0.17 mg QD) Fasted

B = Clonidine IR Tablet (0.1 mg clonidine hydrochloride Q12h) Fasted

C = NEXICLON XR Tablets (0.17 mg QD) Fed

In the multi-dose study, mild to moderate hypertensive patients were randomized to ER and BID IR clonidine formulations. The following plot shows the sitting blood pressure values for each treatment group at Day 22.

The half-life may increase up to 41 hours in patients with severe impairment of renal function. Following oral administration of clonidine about 40 to 60% of the absorbed dose is recovered in the urine as unchanged drug in 24 hours. About 50% of the absorbed dose is metabolized in the liver.

13 NONCLINICAL TOXICOLOGY

13.1 Carcinogenesis, Mutagenesis, Impairment of Fertility

Chronic dietary administration of clonidine was not carcinogenic to rats (132 weeks) or mice (78 weeks) dosed, respectively, at up to 46 or 70 times the maximum recommended daily human dose as mg/kg (9 or 6 times the MRDHD on a mg/m^2 basis). There was no evidence of genotoxicity in the Ames test for mutagenicity or mouse micronucleus test for clastogenicity.

Fertility of male or female rats was unaffected by clonidine doses as high as 150 mcg/kg (approximately 3 times MRDHD). In a separate experiment, fertility of female rats appeared to be affected at dose levels of 500 to 2000 mcg/kg (10 to 40 times the oral MRDHD on a mg/kg basis; 2 to 8 times the MRDHD on a mg/m^2 basis).

13.2 Animal Toxicology and/or Pharmacology

In several studies with oral clonidine hydrochloride, a dose-dependent increase in the incidence and severity of spontaneous retinal degeneration was seen in albino rats treated for six months or longer. Tissue distribution studies in dogs and monkeys showed a concentration of clonidine in the choroid.

In view of the retinal degeneration seen in rats, eye examinations were performed during clinical trials in 908 patients before, and periodically after, the start of clonidine therapy. In 353 of these 908 patients, the eye examinations were carried out over periods of 24 months or longer. Except for some dryness of the eyes, no drug-related abnormal ophthalmological findings were recorded and, according to specialized tests such as electroretinography and macular dazzle, retinal function was unchanged.

In combination with amitriptyline, clonidine hydrochloride administration led to the development of corneal lesions in rats within 5 days.

14 CLINICAL STUDIES

[ see Clinical Pharmacology (12.3)].

16 HOW SUPPLIED/STORAGE AND HANDLING

NEXICLON XR (clonidine) Extended-Release Tablets are scored, splitable, capsule-shaped coated tablets that are supplied in bottles of 30.

Strength | Color | Markings | NDC
0.17 mg | White | NP 2 | 71511-503-30

Store at 20º to 25ºC (68º to 77ºF); excursions permitted to 15º to 30ºC (59º to 86ºF). [See USP Controlled Room Temperature.]

Dispense in a tight, light-resistant container with a child-resistant closure.

17 PATIENT COUNSELING INFORMATION

Caution patients against interruption of NEXICLON XR therapy without their healthcare provider’s advice.

Advise patients who engage in potentially hazardous activities, such as operating machinery or driving, of a possible sedative effect of clonidine. The sedative effect may be increased by concomitant use of alcohol, barbiturates, or other sedating drugs.

Manufactured for:
Athena Bioscience, LLC
Athens, GA 30601

By:
Tris Pharma, Inc.
Monmouth Junction, NJ 08852

08/2021

PACKAGE LABEL PRINCIPAL DISPLAY PANEL

NEXICLON XR® (Clonidine Extended-Release) Tablet